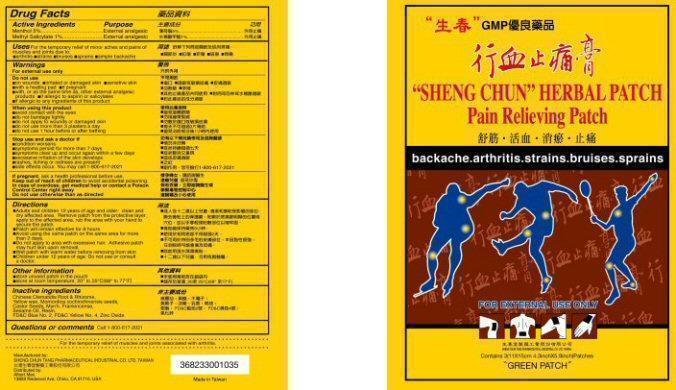 DRUG LABEL: SHENG CHUN HERBAL
NDC: 67473-103 | Form: PATCH
Manufacturer: Sheng Chun Tang Pharmaceutical Industrial Co., Ltd
Category: otc | Type: HUMAN OTC DRUG LABEL
Date: 20140220

ACTIVE INGREDIENTS: MENTHOL 0.05 g/1 g; METHYL SALICYLATE 0.01 g/1 g
INACTIVE INGREDIENTS: CLEMATIS CHINENSIS ROOT; YELLOW WAX; MOMORDICA COCHINCHINENSIS SEED; RICINUS COMMUNIS SEED; MYRRH; FRANKINCENSE; SESAME OIL; PINUS MASSONIANA RESIN; FD&C BLUE NO. 2; FD&C YELLOW NO. 5; ZINC OXIDE

Drug Facts Active Ingredients

Menthol 5%
Methyl Salicylate 1%

Purpose

External analgesic

Keep out of reach of children to avoid accidental poisoning.
In case of overdose, get medical help or contact a Poison Control Center right away.

Uses

For the temporary relief of minor aches and pains of muscles and joints due to:

- arthritis
- strains
- bruises
- sprains
- simple backaches

Warnings

For external use only
Do not use otherwise than as directed.

Do not use

- on wounds
- irritated or damaged skin
- sensitive skin
- with a heating pad
- if pregnant
- with, or as the same time as other external analgesic products
- if allergic to aspirin or salicylates
- if allergic to any ingredients of this product

When using this product

- avoid contact with the eyes
- do not bandage tightly
- do not apply to wounds or damaged skin
- do not use more than 3 plasters a day
- do not use 1 hour before or after bathing

Stop use and ask a doctor if

- condition worsens
- symptoms persist for more than 7 days
- symptoms clear up and occur again within a few days
- excessive irritation of the skin develops
- rashes, itching or redness are present
- side effects occur. You may call: 1-800-617-2021

If pregnant,

ask a health professional before use.

Directions

- Adults and children 12 years of age and older: clean and dry affected area. Remove patch from the protective layer, apply to the affected area, rub the area with your hand to secure the patch.
- Patch will remain effective for 8 hours.
- Avoid using the same patch on the same area for more than 2 days.
- Do not apply to area with excessive hair. Adhesive patch may hurt skin upon removal.
- Wet patch with warm water before removing from skin.
- Children under 12 years of age: Do not use or consult a doctor.

Other Information

- Store unused patch in the pouch
- Store at room temperature, 20 to 25° C (68 to 77° F)

Inactive Ingredients

Chinese Clematidis Root and Rhizome, Yellow wax, Momordica cochinchinensis seeds, Castor Seeds, Myrrh, Frankincense, Sesame Oil, Resin, FD and C Blue No. 2, FD and C Yellow No. 4, Zinc Oxide

Questions or comments

Call 1-800-617-2021

Product Label

GMP

"SHENG CHUN" HERBAL PATCH
Pain Relieving Patch

backache arthritis strains bruises sprains

FOR EXTERNAL USE ONLY

Contains 3(11X15cm 4.3inchX5.9inch)Patches

"GREEN PATCH"

For the temporary relief of muscles and joints associated with arthritis

Manufactured by:
SHENG CHUN TANG PHARMACEUTICAL INDUSTRIAL CO., LTD. TAIWAN

Distributed by:
Albert Max
13859 Redwood Ave. Chino, CA 91710 USA

Made in Taiwan